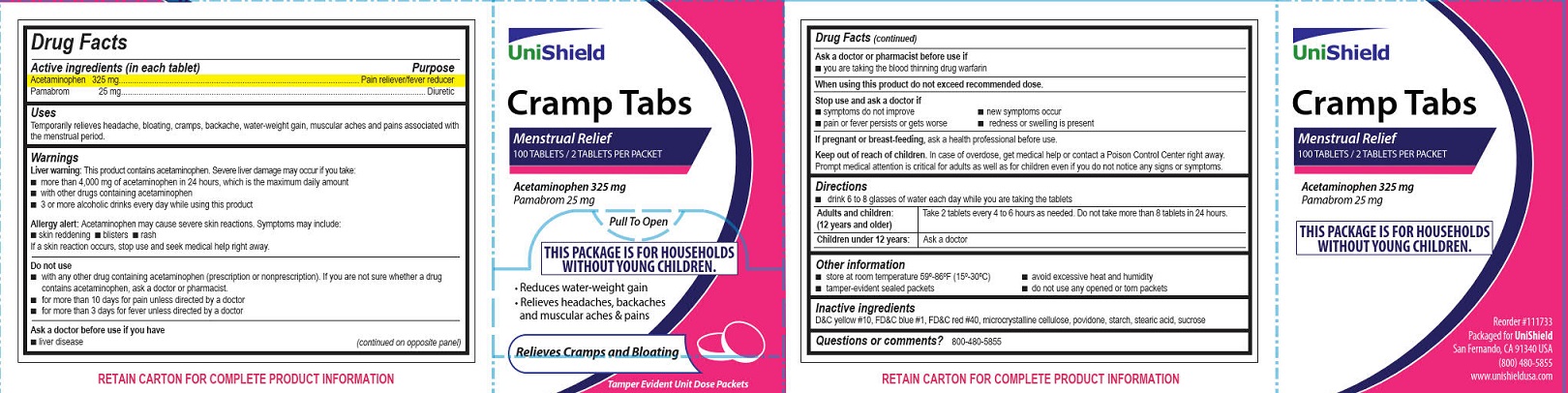 DRUG LABEL: Unishield Cramp
NDC: 49314-8103 | Form: TABLET, FILM COATED
Manufacturer: Unishield
Category: otc | Type: HUMAN OTC DRUG LABEL
Date: 20220316

ACTIVE INGREDIENTS: ACETAMINOPHEN 325 mg/1 1; PAMABROM 25 mg/1 1
INACTIVE INGREDIENTS: CELLULOSE, MICROCRYSTALLINE; D&C YELLOW NO. 10; SUCROSE; FD&C BLUE NO. 1; FD&C RED NO. 40; STARCH, CORN; POVIDONE; STEARIC ACID

Unishield Cramp Tabs

Drug Facts

Active ingredient (in each tablet)

Acetaminophen 325 mg

Pamabrom 25 mg

Purpose

Pain reliever/fever reducer

Diuretic

Uses

Temporarily relieves headache, bloating, cramps, backache, water-weight gain, muscular aches and pains associated with the menstrual period.

Warnings

Liver warning: This product contains acetaminophen. Severe liver damage may occur if you take:

■ more than 4,000 mg of acetaminophen in 24 hours, which is the maximum daily amount

■ with other drugs containing acetaminophen

■ 3 or more alcoholic drinks every day while using this product

Allergy alert: Acetaminophen may cause severe skin reactions. Symptoms may include:

■ skin reddening

■ blisters

■ rash

If a skin reaction occurs, stop use and seek medical help right away.

Do not use

■ with any other drug containing acetaminophen (prescription or nonprescription). If you are not sure
whether a drug contains acetaminophen, ask a doctor or pharmacist.

■ for more than 10 days for pain unless directed by a doctor

■ for more than 3 days for fever unless directed by a doctor

Ask a doctor before use if you have

■ liver disease

Ask a doctor or pharmacist before use if

■ you are taking the blood thinning drug warfarin

When using this product do not exceed recommended dose.

Stop use and ask a doctor if

■ symptoms do not improve

■ new symptoms occur

■ pain or fever persists or gets worse

■ redness or swelling is present

PREGNANCY OR BREAST FEEDING

If pregnant or breast-feeding, ask a health professional before use.

Keep out of reach of children. In case of overdose, get medical help or contact a Poison Control Center right away. Prompt medical attention is critical for adults as well as for children even if you do not notice any signs or symptoms.

Directions

■ drink 6 to 8 glasses of water each day while you are taking the tablets

Adults and children: (12 years and older) Take 2 tablets every 4 to 6 hours as needed.
Do not take more than 8 tablets in 24 hours.

Children under 12 years: Ask a doctor

Other information

■ store at room temperature 59º-86ºF (15º-30ºC)

■ avoid excessive heat and humidity

■ tamper-evident sealed packets

■ do not use any opened or torn packets

Inactive ingredients

D&C yellow #10, FD&C blue #1, FD&C red #40, microcrystalline cellulose,

povidone, starch, stearic acid, sucrose

Questions or comments? 800-480-5856

Unishield Cramp Tabs

Unishield

Cramp Tabs

Menstrual Relief

100 Tablets/ 1 Tablet Per Packet

Acetaminophen 325 mg

Pamabrom 25 mg

Pull To Open

This Package is for Households without Young Children.

• Reduces water-weight gain

• Relieves headaches, backaches and muscular aches & pains

Relieves Cramps and Bloating

Tamper Evident Unit Dose Packets